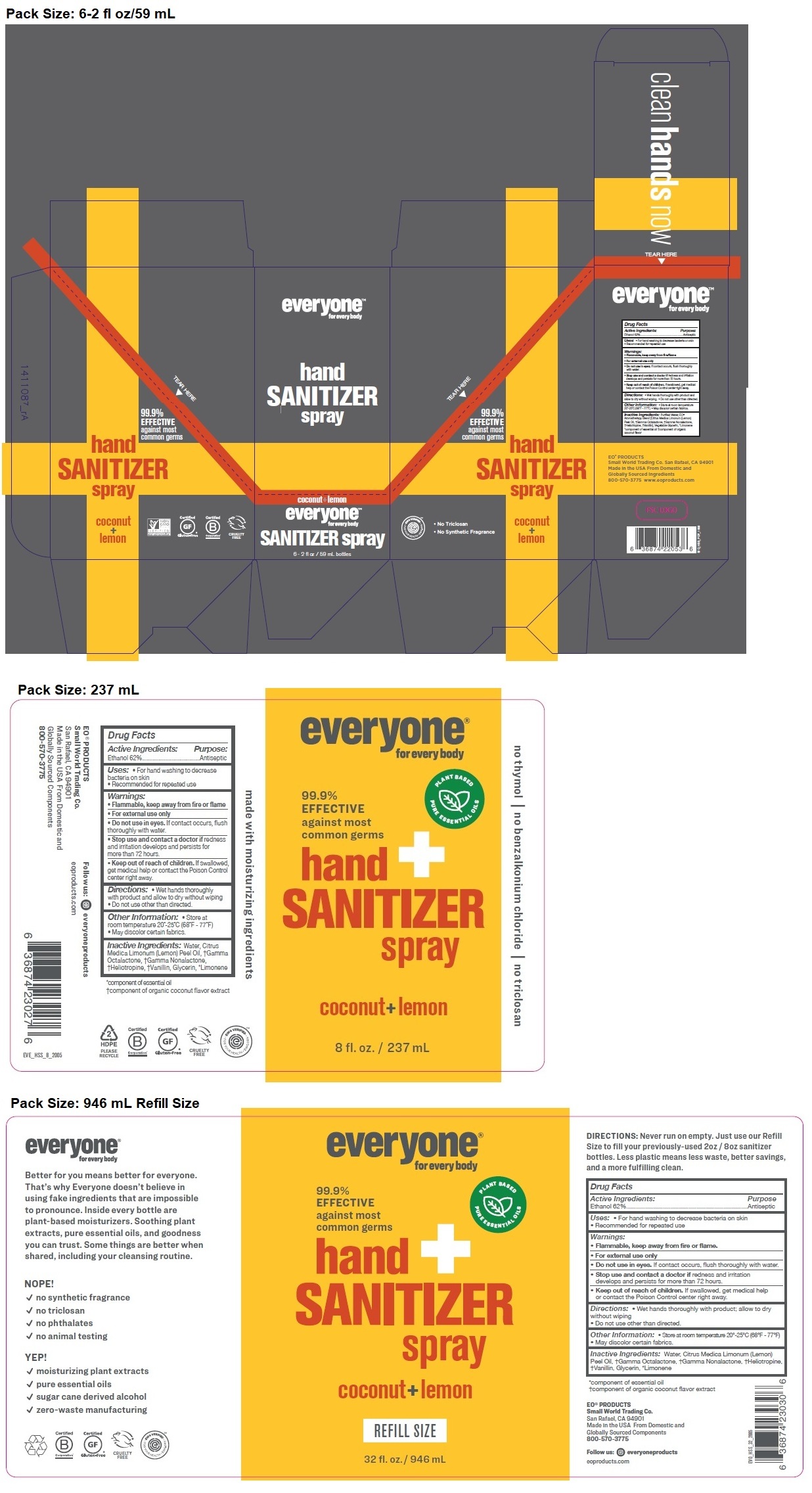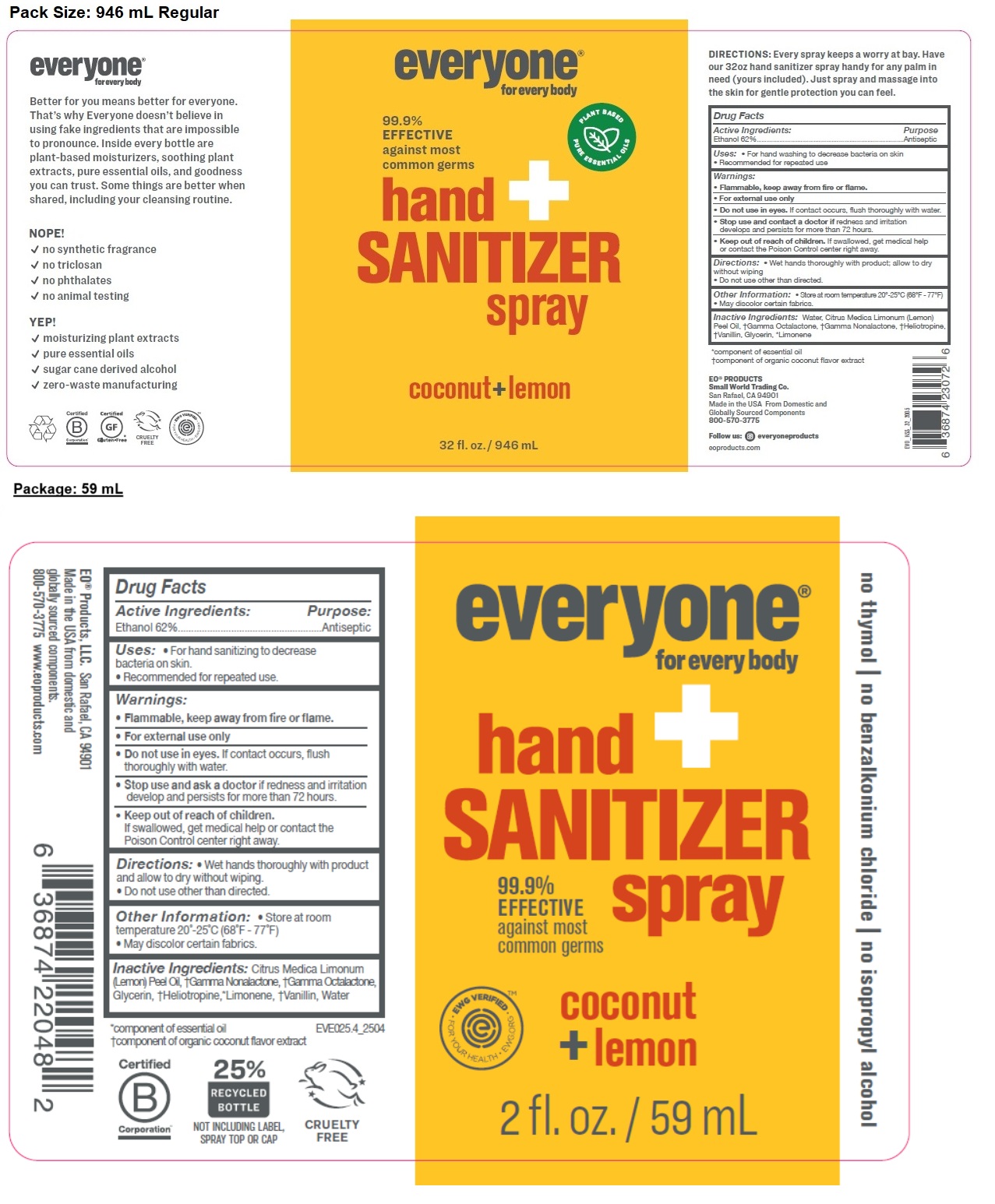 DRUG LABEL: everyone Hand Sanitizer
NDC: 54748-301 | Form: SPRAY
Manufacturer: EO Products, LLC
Category: otc | Type: HUMAN OTC DRUG LABEL
Date: 20251127

ACTIVE INGREDIENTS: ALCOHOL 62 mL/100 mL
INACTIVE INGREDIENTS: LEMON OIL, COLD PRESSED; .GAMMA.-NONALACTONE; .GAMMA.-OCTALACTONE; GLYCERIN; PIPERONAL; LIMONENE, (+)-; VANILLIN; WATER

everyone® for every body hand SANITIZER spray coconut + lemon

Active Ingredients:

Ethanol 62%

Purpose:

Antiseptic

Uses:

- For hand sanitizing to decrease bacteria on skin.
- Recommended for repeated use.

Warnings:

- Flammable, keep away from fire or flame.
- For external use only
- Do not use in eyes. If contact occurs, flush thoroughly with water.
- Stop use and ask a doctor if redness and irritation develop and persists for more than 72 hours.

- Keep out of reach of children.
  If swallowed, get medical help or contact the Poison Control center right away.

Directions:

- Wet hands thoroughly with product and allow to dry without wiping.
- Do not use other than directed.

Other Information:

- Store at room temperature 20°-25°C (68°F - 77°F)
- May discolor certain fabrics.

Inactive Ingredients:

Citrus Medica Limonum (Lemon) Peel Oil, †Gamma Nonalactone, †Gamma Octalactone, Glycerin, †Heliotropine, *Limonene, †Vanillin, Water

*component of essential oil
†component of organic coconut flavor extract

99% EFFECTIVE against most common germs

no thymol | no benzalkonium chloride | no isopropyl alcohol

EO® Products, LLC. San Rafael, CA 94901
Made in the USA from domestic and globally sourced components.
800-570-3775 www.eoproducts.com

CRUELTY FREE